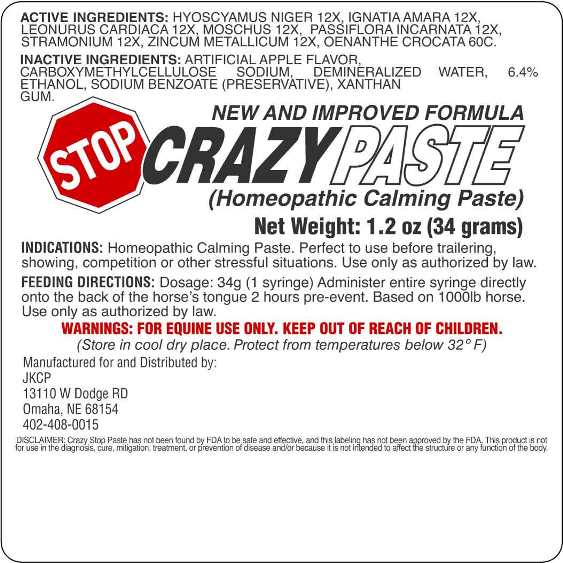 DRUG LABEL: Stop Crazy
NDC: 81829-0001 | Form: PASTE
Manufacturer: JKCP LLC
Category: homeopathic | Type: OTC ANIMAL DRUG LABEL
Date: 20210811

ACTIVE INGREDIENTS: HYOSCYAMUS NIGER 12 [hp_X]/1 g; STRYCHNOS IGNATII SEED 12 [hp_X]/1 g; LEONURUS CARDIACA WHOLE 12 [hp_X]/1 g; MOSCHUS MOSCHIFERUS MUSK SAC RESIN 12 [hp_X]/1 g; PASSIFLORA INCARNATA FLOWERING TOP 12 [hp_X]/1 g; DATURA STRAMONIUM 12 [hp_X]/1 g; ZINC 12 [hp_X]/1 g; OENANTHE CROCATA ROOT 60 [hp_C]/1 g
INACTIVE INGREDIENTS: APPLE; CARBOXYMETHYLCELLULOSE SODIUM; WATER; SODIUM BENZOATE; XANTHAN GUM; ALCOHOL

DRUG FACTS:

ACTIVE INGREDIENTS:

Hyoscyamus Niger 12X, Ignatia Amara 12X, Leonurus Cardiaca 12X, Moschus 12X, Passiflora Incarnata 12X, Stramonium 12X, Zincum Metallicum 12X, Oenanthe Crocata 60C.

INDICATIONS:

Homeopathic Calming Paste. Perfect to use before trailering, showing, competition or other stressful situations. Use only as authorized by law.

WARNINGS:

FOR EQUINE USE ONLY. KEEP OUT OF REACH OF CHILDREN.

(Store in cool dry place. Protect from temperatures below 32 F)

DISCLAIMER: Crazy Stop Paste has not been found by FDA to be safe and effective, and this labeling has not been approved by the FDA. This product is not for use in the diagnosis, cure, mitigation, treatment, or prevention of disease and/or because it is not intended to affect the structure or any function of the body.

KEEP OUT OF REACH OF CHILDREN:

FOR EQUINE USE ONLY. KEEP OUT OF REACH OF CHILDREN.

FEEDING DIRECTIONS:

Dosage: 34g (1 Syringe) Administer entire syringe directly onto the back of the horse's tongue 2 hours pre-event. Based on 1000lb horse.

Use only as authorized by law.

INDICATIONS:

Homeopathic Calming Paste. Perfect to use before trailering, showing, competition or other stressful situations. Use only as authorized by law.

INACTIVE INGREDIENTS:

Artificial Apple Flavor, Carboxymethylcellulose Sodium, Demineralized Water, 6.4% Ethanol, Sodium Benzoate, Xanthan Gum.

QUESTIONS:

Manufactured for and Distributed by:

JKCP

13110 W Dodge RD

Omaha, NE 68154

402-408-0015

PACKAGE LABEL DISPLAY:

NEW AND IMPROVED FORMULA

STOP CRAZY PASTE

(Homeopathic Calming Paste)

Net Weight: 1.2 oz (34 grams)